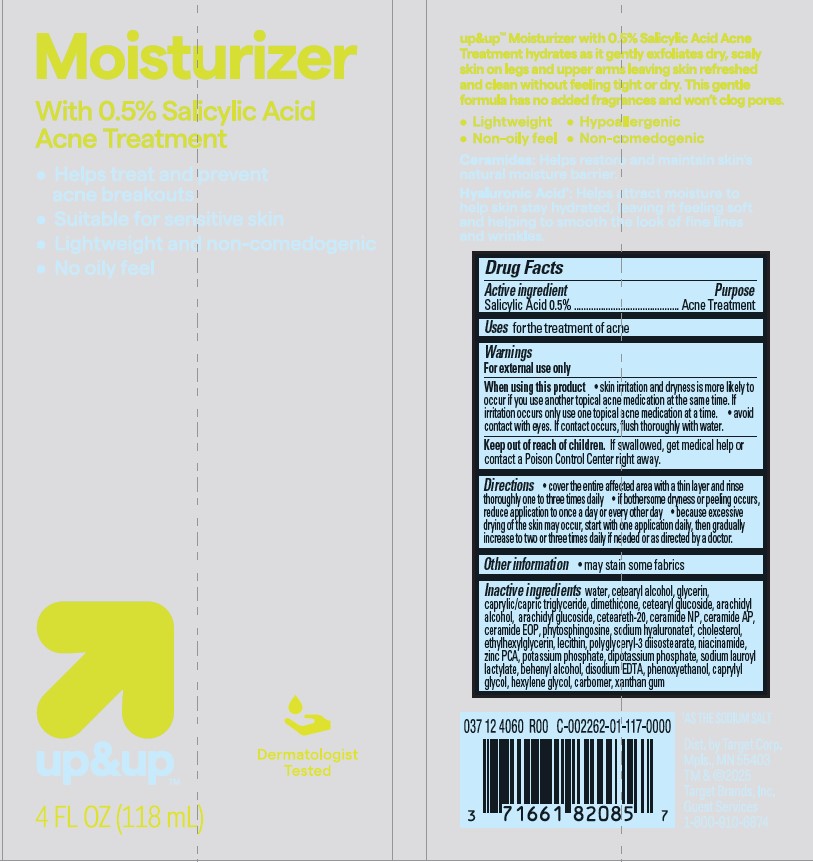 DRUG LABEL: Target Up and Up Moisturizer with Salicylic Acid Acne Treatment
NDC: 82442-016 | Form: LOTION
Manufacturer: TARGET CORPORATION
Category: otc | Type: HUMAN OTC DRUG LABEL
Date: 20240930

ACTIVE INGREDIENTS: SALICYLIC ACID 5 mg/1 mL
INACTIVE INGREDIENTS: ZINC PIDOLATE; HEXAMETHYLDISILOXANE; NIACINAMIDE; DOCOSANOL; POLYOXYL 20 CETOSTEARYL ETHER; HEXYLENE GLYCOL; CETOSTEARYL ALCOHOL; EDETATE DISODIUM; DIBASIC POTASSIUM PHOSPHATE; POTASSIUM PHOSPHATE, UNSPECIFIED FORM; CERAMIDE AP; WATER; CHOLESTEROL; PHYTOSPHINGOSINE; GLYCERIN; ETHYLHEXYLGLYCERIN; XANTHAN GUM; HYALURONATE SODIUM; MEDIUM-CHAIN TRIGLYCERIDES; CAPRYLYL GLYCOL; PHENOXYETHANOL; LECITHIN, SOYBEAN; ARACHIDYL GLUCOSIDE; CETEARYL GLUCOSIDE; SODIUM LAUROYL LACTYLATE; CERAMIDE NP; POLYACRYLIC ACID (250000 MW); POLYGLYCERYL-3 DIISOSTEARATE; ARACHIDYL ALCOHOL

Target Up and Up Moisturizer with Salicylic Acid Acne Treatment

Active Ingredient

Salicylic Acid 0.5%

Purpose

Acne Treatment

Uses

for the treatment of acne

Warnings

For external use only.

When using this product

- skin irritation and dryness are more likely to occur when using another topical acne product at the same time. If irritation occurs, use only one acne product at a time.
- avoid contact with eyes. If contact occurs, flush thoroughly with water.

Keep out of reach of children.

If swallowed, seek medical help or contact a Poison Control Center right away.

Directions

- cover the entire affected area with a thin layer and rinse thoroughly one to three times daily.
- if bothersome dryness or peeling occurs, reduce application to once a day or every other day.
- because excessive drying of the skin may occur, start with one application daily, then gradually increase to two or three times daily if needed or as directed by a doctor.

Other Information

- may stain some fabrics

Inactive Ingredients

water, cetearyl alcohol, glycerin,
caprylic/capric triglyceride, dimethicone, cetearyl glucoside, arachidyl
alcohol, arachidyl glucoside, ceteareth-20, ceramide NP, ceramide AP,
ceramide EOP, phytosphingosine, sodium hyaluronate†, cholesterol,
ethylhexylglycerin, lecithin, polyglyceryl-3 diisostearate, niacinamide,
zinc PCA, potassium phosphate, dipotassium phosphate, sodium lauroyl
lactylate, behenyl alcohol, disodium EDTA, phenoxyethanol, caprylyl
glycol, hexylene glycol, carbomer, xanthan gum